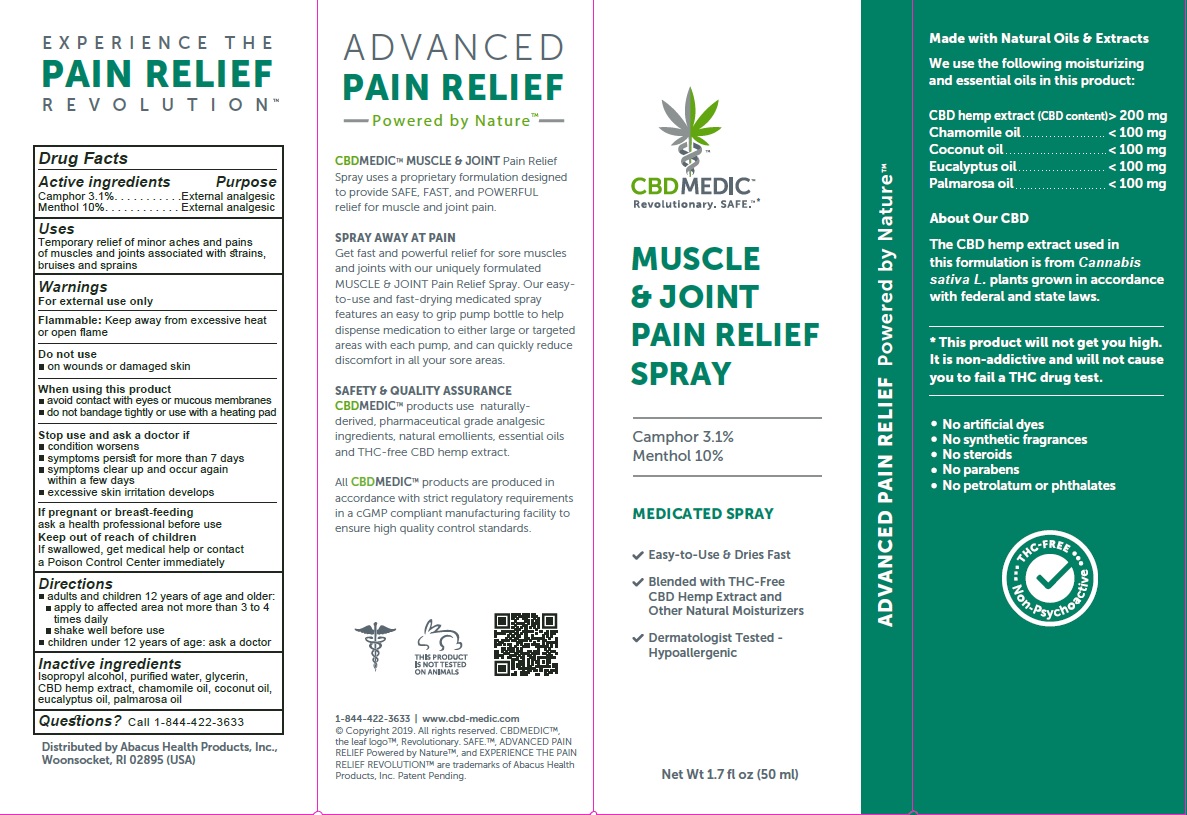 DRUG LABEL: CBDMEDIC Muscle and Joint Pain Relief
NDC: 24909-748 | Form: SPRAY
Manufacturer: AIDANCE SKINCARE & TOPICAL SOLUTIONS, LLC
Category: otc | Type: HUMAN OTC DRUG LABEL
Date: 20191225

ACTIVE INGREDIENTS: CAMPHOR (NATURAL) 31 mg/1 mL; MENTHOL 100 mg/1 mL
INACTIVE INGREDIENTS: COCONUT OIL; CHAMOMILE FLOWER OIL; EUCALYPTUS OIL; GLYCERIN; HEMP; ISOPROPYL ALCOHOL; PALMAROSA OIL; WATER

CBDMEDIC Muscle and Joint Pain Relief

Active Ingredients and Purpose

Camphor 3.1%, Menthol 10% (External Analgesics)

Uses

Temporary relief of minor aches and pains of muscles and joints associated with strains, bruises and sprains

Warnings

For external use only
Flammable: Keep away from excessive heat or open flame
Do not use on
• wounds or damaged skin
When using this product
• avoid contact with eyes or mucous membranes
• do not bandage tightly or use with a heating pad
Stop use and ask a doctor if
• condition worsens
• symptoms persist for more than 7 days
• symptoms clear up and occur again within a few days
• excessive skin irritation develops
If pregnant or breast-feeding
ask a health professional before use
Keep out of reach of children
If swallowed, get medical help or contact a Poison Control Center immediately

Directions

Adults and children 12 years of age and older:
• apply to affected area not more than 3 to 4 times daily
• shake well before use
Children under 12 years of age: ask a doctor

Inactive ingredients

Isopropyl alcohol, purified water, glycerin, CBD hemp extract, chamomile oil, coconut oil, eucalyptus oil, palmarosa oil

Questions?

Call 1-844-422-3633